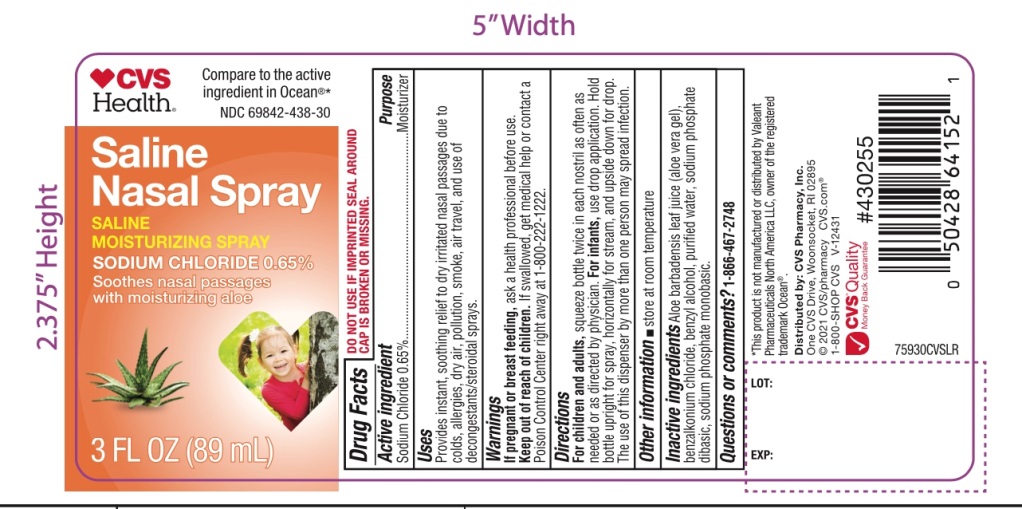 DRUG LABEL: CVS Saline
NDC: 69842-438 | Form: SPRAY
Manufacturer: CVS PHARMACY
Category: otc | Type: HUMAN OTC DRUG LABEL
Date: 20251210

ACTIVE INGREDIENTS: SODIUM CHLORIDE 6.5 mg/1 mL
INACTIVE INGREDIENTS: ALOE VERA LEAF; BENZALKONIUM CHLORIDE; BENZYL ALCOHOL; WATER; SODIUM PHOSPHATE, DIBASIC, UNSPECIFIED FORM; SODIUM PHOSPHATE, MONOBASIC, UNSPECIFIED FORM

Saline Nasal Spray

Drug Facts Active Ingredients

Sodium Chloride 0.65%

Purpose

Moisturizer

Uses

provides instant, soothing relief to dry irritated nasal passages due to colds, allergies, dry air, pollution, smoke, air travel and use of decongestants/steroidal sprays.

Warnings

If pregnant or breast-feeding, ask a healthcare professional before use.

Keep out of reach of children.

If swallowed, get medical help or contact a Poison Control Center right away at 1-800-222-1222

Directions

For children and adults,squeeze bottle twice in each nostril as often as needed or as directed by physician. For infants,use drop application. Hold bottle upright for spray, horizontally for stream, and upside down for drop. The use of this dispenser by more than one person may spread infection.

Other Information

- store at room temperature

Inactive Ingredients

Aloe barbadensis leaf juice (aloe vera gel), benzalkonium chloride, benzyl alcohol, purified water, sodium phosphate dibasic, sodium phosphate monobasic

Questions or comments?

1-866-467-2748

*This product is not manufactured or distributed by Valeant Pharmaceuticals North America LLC, owners of the registered trademark Ocean®.

Distributed by:

Saline Nasal Spray

Compare to the ingredient in Ocean®*

NDC: 69842-438-30

Saline Nasal Spray

+Soothing Aloe

Sodium Chloride 0.65%

- Instantly relieves dry nasal passages caused by sinus, cold and allergy medications and dry air
- Gentle enough for infants
- Relief for stuffy noses

3 FL O.Z. (89 mL)

TAMPER EVIDENT: DO NOT USE IF IMPRINTED SEAL AROUND CAP IS BROKEN OR MISSING.

Distributed by: